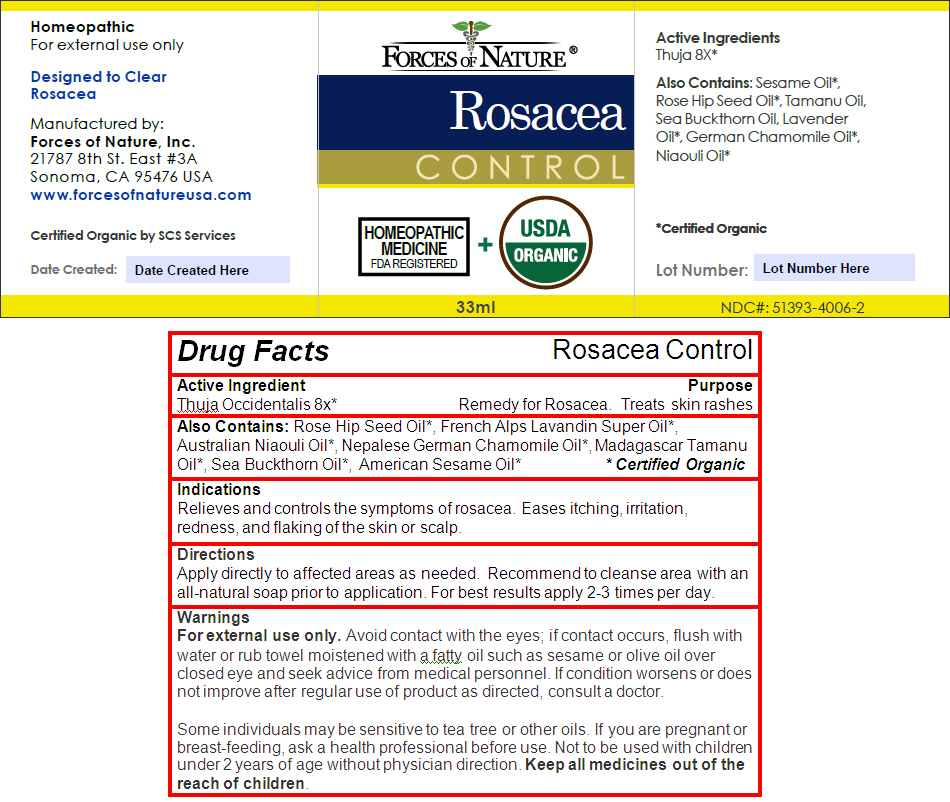 DRUG LABEL: ROSACEA
NDC: 51393-4006 | Form: SOLUTION/ DROPS
Manufacturer: Forces of Nature
Category: homeopathic | Type: HUMAN OTC DRUG LABEL
Date: 20200428

ACTIVE INGREDIENTS: THUJA OCCIDENTALIS LEAFY TWIG 8 [hp_X]/1000 mL
INACTIVE INGREDIENTS: Lavender Oil; Rosa Moschata Oil; MELALEUCA QUINQUENERVIA LEAF OIL; Chamomile Flower Oil; Tamanu Oil; HIPPOPHAE RHAMNOIDES FRUIT OIL; Sesame Oil

ROSACEA

Drug Facts

Active Ingredient

Thuja Occidentalis 8x [Certified Organic]

Purpose

Remedy for Rosacea. Treats skin rashes.

Also Contains

Rose Hip Seed Oil, French Alps Lavandin Super Oil, Australian Niaouli Oil, Nepalese German Chamomile Oil, Madagascar Tamanu Oil, Sea Buckthorn Oil, American Sesame Oil

Indications

Relieves and controls the symptoms of rosacea. Eases itching, irritation, redness, and flaking of the skin or scalp.

Directions

Apply directly to affected areas as needed. Recommend to cleanse area with an all-natural soap prior to application. For best results apply 2-3 times per day.

Warnings

For External Use Only. Avoid contact with the eyes; if contact occurs, flush with water or rub towel moistened with a fatty oil such as sesame or olive oil over closed eye and seek advice from medical personnel.

ASK DOCTOR

If condition worsens or does not improve after regular use of product as directed, consult a doctor.

Some individuals may be sensitive to tea tree or other oils.

PREGNANCY OR BREAST FEEDING

If you are pregnant or breastfeeding, ask a health professional before use.

DO NOT USE

Not to be used with children under 2 years of age without physician direction.

KEEP OUT OF REACH OF CHILDREN

Keep all medicines out of the reach of children.

PRINCIPAL DISPLAY PANEL - 33 ml Bottle Label

FORCES OF NATURE ®

Rosacea
CONTROL

HOMEOPATHIC
MEDICINE
FDA REGISTERED
+
USDA
ORGANIC

33ml